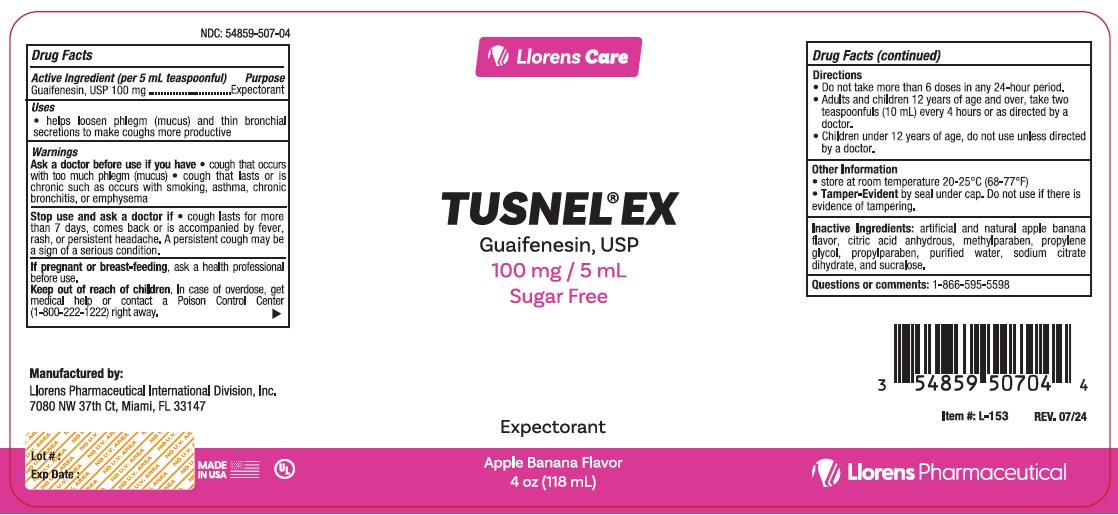 DRUG LABEL: Tusnel
NDC: 54859-507 | Form: LIQUID
Manufacturer: Llorens Pharmaceutical International Division, Inc.
Category: otc | Type: HUMAN OTC DRUG LABEL
Date: 20251229

ACTIVE INGREDIENTS: GUAIFENESIN 100 mg/5 mL
INACTIVE INGREDIENTS: ANHYDROUS CITRIC ACID; METHYLPARABEN; PROPYLENE GLYCOL; PROPYLPARABEN; WATER; TRISODIUM CITRATE DIHYDRATE; SUCRALOSE

Llorens-TusnelEX 507

ACTIVE INGREDIENT

In each 5 mL

Guaifenesin - 100 mg

Purpose

Expectorant

Uses

- temporarily relieves cough due to minor thraot and bronchial irritations as may occur with a cold
- helps loosen phlegm (mucus) and thin bronchial secretions to make coughs more productive

Warnings

Do not use if you are now taking a prescritpion monamine oxidase inhibitor (MAOI) (certain drugs for depression, psychiatric, or emotional conditions, or Parkinson's diesease), or for 2 weeks after stopping the MAOI drug. If you do not know if your prescirption drug contains an MAOI, aska doctor or pharmacist before taking this product.

Ask a doctor before use if you have

- cough that occurs with too much phlegm (mucus)
- cough that lasts or is chronic such as occurs with smoking, asthma, chronic bronchitis, or emphysema

Stop use and ask a doctor if cough lasts for more than 7 days, comes back, or is accompanied by fever, rash, or persistent headache. A persistent cough may be a sign of a serious condition.

PREGNANCY OR BREAST FEEDING

If pregnant or breast-feeing, ask a health professional before use.

Keep out of reach of children. In case of overdose, get medical help or contact a Poison Control Center right away.

DOSAGE AND ADMINISTRATION

Directions: Do not exceed more than 6 doses in any 24-hour period.

Age | Dose
Adults and children over 12 years and over | 2 teaspoonfuls (10 mL) every 4 hours
Children under 12 years | Ask a doctor

INACTIVE INGREDIENT

Inactive ingredients anhydrous citric acid, flavor, methylparaben, propylene glycol, propylparaben, purified water, sodium citrate digydrate, and a sucralose.

Questions or comments? 1-8660595-5598